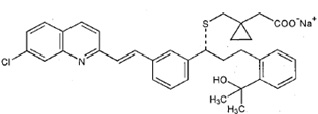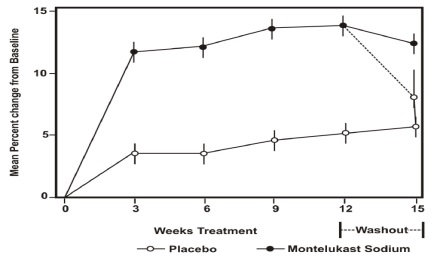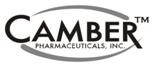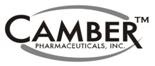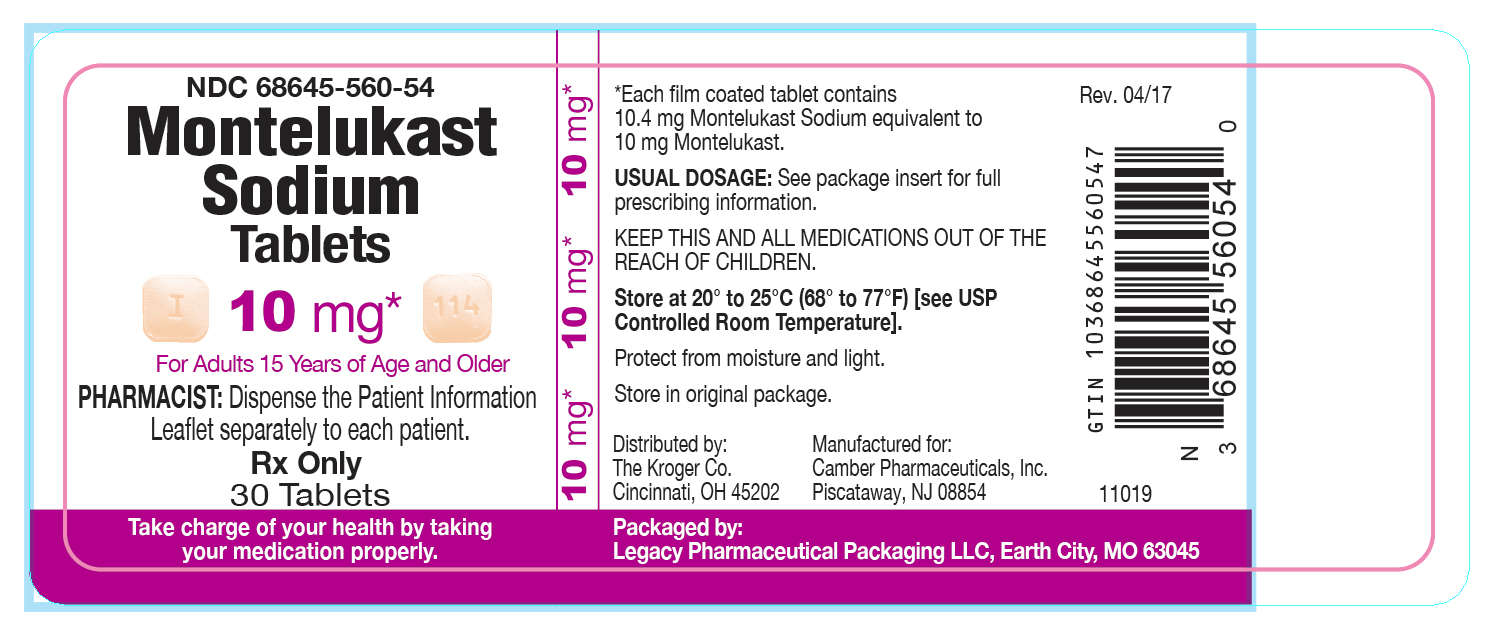 DRUG LABEL: Montelukast
NDC: 68645-560 | Form: TABLET, FILM COATED
Manufacturer: Legacy Pharmaceutical Packaging, LLC
Category: prescription | Type: HUMAN PRESCRIPTION DRUG LABEL
Date: 20251231

ACTIVE INGREDIENTS: MONTELUKAST SODIUM 10 mg/1 1
INACTIVE INGREDIENTS: HYDROXYPROPYL CELLULOSE (1600000 WAMW); CROSCARMELLOSE SODIUM; LACTOSE MONOHYDRATE; MAGNESIUM STEARATE; MANNITOL; CELLULOSE, MICROCRYSTALLINE; CARNAUBA WAX; HYPROMELLOSES; FERRIC OXIDE RED; TITANIUM DIOXIDE; FERRIC OXIDE YELLOW

HIGHLIGHTS OF PRESCRIBING INFORMATION

These highlights do not include all the information needed to use MONTELUKAST SODIUM TABLETS safely and effectively. See full prescribing information for MONTELUKAST SODIUM TABLETS.
MONTELUKAST Sodium Tablets for oral use
Initial U.S. Approval: 1998

RECENT MAJOR CHANGES

Boxed Warning 04/2020
Indications and Usage, Allergic Rhinitis (1.3) 04/2020
Dosage and Administration, Asthma (2.1),
Allergic Rhinitis (2.3), Asthma and Allergic Rhinitis (2.4) 04/2020
Warnings and Precautions, Neuropsychiatric Events (5.1) 04/2020

1 INDICATIONS & USAGE

Montelukast sodium tablet is a leukotriene receptor antagonist indicated for:

•Prophylaxis and chronic treatment of asthma in patients 15 years of age and older (1.1).
•Acute prevention of exercise-induced bronchoconstriction (EIB) in patients 15 years of age and older (1.2).
•Relief of symptoms of allergic rhinitis (AR): seasonal allergic rhinitis (SAR) in patients 15 years of age and older, and perennial allergic rhinitis (PAR) in patients 15 years of age and older (1.3). Reserve use for patients
who have an inadequate response or intolerance to alternative therapies (1.3).

2 DOSAGE AND ADMINISTRATION

Administration (by indications):

• Asthma (2.1): Once daily in the evening for patients 15 years of age and older.

• Acute prevention of EIB (2.2): One tablet at least 2 hours before exercise for patients 15 years of age and older.

• Seasonal allergic rhinitis (2.3): Once daily for patients 15 years of age and older.

• Perennial allergic rhinitis (2.3): Once daily for patients 15 years of age and older.
Dosage (by age) (2):

• 15 years and older: one 10 mg tablet.

Patients with both asthma and allergic rhinitis should take only one dose daily in the evening (2.4).

3 DOSAGE FORMS & STRENGTHS

• Tablets: 10 mg (3)

4 CONTRAINDICATIONS

•Hypersensitivity to any component of this product (4).

5 WARNINGS AND PRECAUTIONS

•Do not prescribe montelukast sodium tablets to treat an acute asthma attack (5.2).

•Advise patients to have appropriate rescue medication available (5.2).

•Inhaled corticosteroid may be reduced gradually. Do not abruptly substitute montelukast sodium tablets for inhaled or oral corticosteroids (5.3).

•Patients with known aspirin sensitivity should continue to avoid aspirin or non-steroidal anti-inflammatory agents while taking montelukast sodium tablets (5.4).

•Systemic eosinophilia, sometimes presenting with clinical features of vasculitis consistent with Churg-Strauss syndrome, has been reported.These events have been sometimes associated with the reduction of oral corticosteroid therapy (5.5and 6.2).

6 ADVERSE REACTIONS

Most common adverse reactions (incidence ≥5% and greater than placebo listed in descending order of frequency): upper respiratory infection, fever, headache, pharyngitis, cough, abdominal pain, diarrhea, otitis media, influenza, rhinorrhea, sinusitis, otitis (6.1).

To report SUSPECTED ADVERSE REACTIONS, contact Hetero Labs Limited at 866-495-1995 or FDA at 1-800-FDA-1088 or www.fda.gov/medwatch.

FULL PRESCRIBING INFORMATION

1 INDICATIONS & USAGE

1.1 Asthma

Montelukast sodium tablet is indicated for the prophylaxis and chronic treatment of asthma in adults and adolescent patients 15 years of age and older.

1.2 Exercise-Induced Bronchoconstriction (EIB)

Montelukast sodium tablet is indicated for prevention of exercise-induced bronchoconstriction (EIB) in patients 15 years of age and older.

1.3 Allergic Rhinitis

Montelukast sodium tablets are indicated for the relief of symptoms of seasonal allergic rhinitis in patients 15 years of age and older and perennial allergic rhinitis in patients 15 years of age and older. Because the benefits of montelukast sodium tablets may not outweigh the risk of neuropsychiatric symptoms in patients with allergic rhinitis [see Warnings and Precautions (5.1)], reserve use for patients who have an inadequate response or intolerance to alternative therapies.

2 DOSAGE AND ADMINISTRATION

2.1 Asthma

Montelukast sodium tablets should be taken once daily in the evening. The following doses are recommended: For adults and adolescents 15 years of age and older: one 10 mg tablet. Safety and effectiveness in pediatric patients less than 12 months of age with asthma have not been established. who miss a dose should take the next dose at their regular time and should not take 2 doses at the same time. There have been no clinical trials in patients with asthma to evaluate the relative efficacy of morning versus evening dosing. The pharmacokinetics of montelukast are similar whether dosed in the morning or evening. Efficacy has been demonstrated for asthma when montelukast was administered in the evening without regard to time of food ingestion. Montelukast sodium tablets should be taken once daily in the evening. The following doses are recommended:
For adults and adolescents 15 years of age and older: one 10 mg tablet.

2.2 Exercise-lnduced Bronchoconstriction (EIB)

For prevention of EIB, a single 10 mg dose of montelukast sodium tablet should be taken at least 2 hours before exercise.

The following doses are recommended:

For adults and adolescents 15 years of age and older: one 10 mg tablet.

An additional dose of montelukast sodium tablet should not be taken within 24 hours of a previous dose. Patients already taking montelukast sodium tablet daily for another indication (including chronic asthma) should not take an additional dose to prevent EIB. All patients should have available for rescue a short-acting β-agonist. Safety and efficacy in patients younger than 15 years of age have not been established. Daily administration of montelukast sodium tablet for the chronic treatment of asthma has not been established to prevent acute episodes of EIB.

2.3 Allergic Rhinitis

For allergic rhinitis, montelukast sodium tablets should be taken once daily. Efficacy was demonstrated for seasonal allergic rhinitis when montelukast was administered in the morning or the evening without regard to time of food ingestion. The time of administration may be individualized to suit patient needs. The following doses for the treatment of symptoms of seasonal allergic rhinitis are recommended: For adults and adolescents 15 years of age and older: one 10 mg tablet. Safety and effectiveness in pediatric patients younger than 2 years of age with seasonal allergic rhinitis have not been established. The following doses for the treatment of symptoms of perennial allergic rhinitis are recommended: For adults and adolescents 15 years of age and older: one 10 mg tablet. Safety and effectiveness in pediatric patients younger than 6 months of age with perennial allergic rhinitis have not been established. who miss a dose should take the next dose at their regular time and should not take 2 doses at the same time. For allergic rhinitis, montelukast sodium tablets should be taken once daily. Efficacy was demonstrated for seasonal allergic rhinitis when montelukast was administered in the morning or the evening without regard to time of food ingestion. The time of administration may be individualized to suit patient needs.
The following doses for the treatment of symptoms of seasonal allergic rhinitis are recommended:
For adults and adolescents 15 years of age and older: one 10 mg tablet.
Safety and effectiveness in pediatric patients younger than 2 years of age with seasonal allergic rhinitis have not been established.
The following doses for the treatment of symptoms of perennial allergic rhinitis are recommended:
For adults and adolescents 15 years of age and older: one 10 mg tablet.
Safety and effectiveness in pediatric patients younger than 6 months of age with perennial allergic rhinitis have not been established.
Patients who miss a dose should take the next dose at their regular time and should not take 2 doses at the same time.

2.4 Asthma and Allergic Rhinitis

Patients with both asthma and allergic rhinitis should take only one montelukast sodium tablets dose daily in the evening. who miss a dose should take the next dose at their regular time and should not take 2 doses at the same time. Patients with both asthma and allergic rhinitis should take only one montelukast sodium tablets dose daily in the evening.
Patients who miss a dose should take the next dose at their regular time and should not take 2 doses at the same time.

3 DOSAGE FORMS & STRENGTHS

• Montelukast sodium film-coated tablets, USP 10 mg are beige, rounded square-shaped, film- coated tablets debossed with 'I' on one side and '114' on the other side.

4 CONTRAINDICATIONS

- Hypersensitivity to any component of this product.

5 WARNINGS AND PRECAUTIONS

5.1 Neuropsychiatric Events

Serious neuropsychiatric (NP) events have been reported with use of montelukast sodium. These postmarketing reports have been highly variable and included, but were not limited to, agitation, aggressive behavior or hostility, anxiousness, depression, disorientation, disturbance in attention, dream abnormalities, dysphemia (stuttering), hallucinations, insomnia, irritability, memory impairment, obsessive-compulsive symptoms, restlessness, somnambulism, suicidal thoughts and behavior (including suicide), tic, and tremor. NP events have been reported in adult, adolescent, and pediatric patients with and without a previous history of psychiatric disorder. NP events have been reported mostly during montelukast sodium treatment, but some were reported after montelukast sodium discontinuation. Animal studies showed that montelukast distributes into the brain in rats [see Clinical Pharmacology (12.3)]; however, the mechanisms underlying montelukast sodium-associated NP events are currently not well understood. Based upon the available data, it is difficult to identify risk factors for or quantify the risk of NP events with montelukast sodium use.

Because of the risk of NP events, the benefits of montelukast sodium may not outweigh the risks in some patients, particularly when the symptoms of disease may be mild and adequately treated with alternative therapies. Reserve use of montelukast sodium for patients with allergic rhinitis who have an inadequate response or intolerance to alternative therapies [see Indications and Usage (1.3)]. In patients with asthma or exercise-induced bronchoconstriction, consider the benefits and risks before prescribing montelukast sodium.

Discuss the benefits and risks of montelukast sodium use with patients and caregivers when prescribing montelukast sodium. Advise patients and/or caregivers to be alert for changes in behavior or for new NP symptoms when taking montelukast sodium. If changes in behavior are observed, or if new NP symptoms or suicidal thoughts and/or behavior occur, advise patients to discontinue montelukast sodium and contact a healthcare provider immediately. In many cases, symptoms resolved after stopping montelukast sodium therapy; however, in some cases symptoms persisted after discontinuation of montelukast sodium. Therefore, continue to monitor and provide supportive care until symptoms resolve. Re-evaluate the benefits and risks of restarting treatment with montelukast sodium if such events occur.

5.2 Acute Asthma

Montelukast sodium tablet is not indicated for use in the reversal of bronchospasm in acute asthma attacks, including status asthmaticus. Patients should be advised to have appropriate rescue medication available. Therapy with montelukast sodium tablet can be continued during acute exacerbations of asthma. Patients who have exacerbations of asthma after exercise should have available for rescue a short-acting inhaled β-agonist.

5.3 Concomitant Corticosteroid Use

While the dose of inhaled corticosteroid may be reduced gradually under medical supervision, montelukast sodium tablet should not be abruptly substituted for inhaled or oral corticosteroids.

5.4 Aspirin Sensitivity

Patients with known aspirin sensitivity should continue avoidance of aspirin or non-steroidal anti-inflammatory agents while taking montelukast sodium tablets. Although montelukast sodium tablets are effective in improving airway function in asthmatics with documented aspirin sensitivity, it has not been shown to truncate bronchoconstrictor response to aspirin and other non-steroidal anti-inflammatory drugs in aspirin-sensitive asthmatic patients [see Clinical Studies (14.1)].

5.5 Eosinophilic Conditions

Patients with asthma on therapy with montelukast sodium tablets may present with systemic eosinophilia, sometimes presenting with clinical features of vasculitis consistent with Churg-Strauss syndrome, a condition which is often treated with systemic corticosteroid therapy. These events have been sometimes associated with the reduction of oral corticosteroid therapy. Physicians should be alert to eosinophilia, vasculitic rash, worsening pulmonary symptoms, cardiac complications, and/or neuropathy presenting in their patients. A causal association between montelukast sodium tablets and these underlying conditions has not been established [see Adverse Reactions (6.2)] .

6 ADVERSE REACTIONS

6.1 Clinical Trials Experience

Because clinical trials are conducted under widely varying conditions, adverse reaction rates observed in the clinical trials of a drug cannot be directly compared to rates in the clinical trials of another drug and may not reflect the rates observed in clinical practice. In the following description of clinical trials experience, adverse reactions are listed regardless of causality assessment.

The most common adverse reactions (incidence ≥5% and greater than placebo; listed in descending order of frequency) in controlled clinical trials were: upper respiratory infection, fever, headache, pharyngitis, cough, abdominal pain, diarrhea, otitis media, influenza, rhinorrhea, sinusitis, otitis.
Adults and Adolescents 15 Years of Age and Older with Asthma
Montelukast sodium tablets have been evaluated for safety in approximately 2950 adult and adolescent patients 15 years of age and older in clinical trials. In placebo-controlled clinical trials, the following adverse experiences reported with montelukast sodium tablets occurred in greater than or equal to 1% of patients and at an incidence greater than that in patients treated with placebo:
Table 1: Adverse Experiences Occurring in ≥1% of Patientswith an Incidence Greater than that in Patients Treated with Placebo

 | Montelukast sodium tablets (equivalent to10 mg montelukast/day) (%) (n=1955) | Placebo (%) (n=1180)
Body As A Whole
Pain, abdominal | 2.9 | 2.5
Asthenia/fatigue | 1.8 | 1.2
Fever | 1.5 | 0.9
Trauma Digestive System Disorders Dyspepsia | 1.0 2.1 | 0.8
Trauma Digestive System Disorders Dyspepsia | 1.0 2.1 | 1.1
Pain, dental | 1.7 | 1.0
Gastroenteritis, infectious | 1.5 | 0.5
Nervous System/Psychiatric
Headache | 18.4 | 18.1
Dizziness | 1.9 | 1.4
Respiratory System Disorders
Influenza | 4.2 | 3.9
Cough | 2.7 | 2.4
Congestion, nasal | 1.6 | 1.3
Skin/Skin Appendages Disorder
Rash | 1.6 | 1.2
Laboratory Adverse Experiences* | 2.1 | 2.0
ALT increased | 1.6 | 1.2
AST increased | 1.0 | 0.9
Pyuria

*Number of patients tested (montelukast sodium tablets and placebo, respectively): ALT and AST, 1935, 1170; pyuria, 1924, 1159.

The frequency of less common adverse events was comparable between montelukast sodium tablets and placebo.

The safety profile of montelukast sodium tablets, when administered as a single dose for prevention of EIB in adult and adolescent patients 15 years of age and older, was consistent with the safety profile previously described for montelukast sodium tablets.

Cumulatively, 569 patients were treated with montelukast sodium tablets for at least 6 months, 480 for one year, and 49 for two years in clinical trials. With prolonged treatment, the adverse experience profile did not significantly change.

Adults and Adolescents 15 Years of Age and Older with Seasonal Allergic Rhinitis

Montelukast sodium tablets have been evaluated for safety in 2199 adult and adolescent patients 15 years of age and older in clinical trials. Montelukast sodium tablets administered once daily in the morning or in the evening had a safety profile similar to that of placebo. In placebo-controlled clinical trials, the following event was reported with montelukast sodium tablets with a frequency ≥1 % and at an incidence greater than placebo: upper respiratory infection, 1.9% of patients receiving montelukast sodium tablets vs. 1.5% of patients receiving placebo. In a 4-week, placebo-controlled clinical study, the safety profile was consistent with that observed in 2-week studies. The incidence of somnolence was similar to that of placebo in all studies.

Adults and Adolescents 15 Years of Age and Older with Perennial Allergic Rhinitis

Montelukast sodium tablets have been evaluated for safety in 3357 adult and adolescent patients 15 years of age and older with perennial allergic rhinitis of whom 1632 received montelukast sodium tablets in two, 6-week, clinical studies. Montelukast sodium tablets administered once daily had a safety profile consistent with that observed in patients with seasonal allergic rhinitis and similar to that of placebo. In these two studies, the following events were reported with montelukast sodium tablets with a frequency ≥1 % and at an incidence greater than placebo: sinusitis, upper respiratory infection, sinus headache, cough, epistaxis, and increased ALT. The incidence of somnolence was similar to that of placebo.

6.2 Post-Marketing Experience

The following adverse reactions have been identified during post-approval use of montelukast sodium tablets. Because these reactions are reported voluntarily from a population of uncertain size, it is not always possible to reliably estimate their frequency or establish a causal relationship to drug exposure.

Blood and lymphatic system disorders: increased bleeding tendency, thrombocytopenia.

Immune system disorders: hypersensitivity reactions including anaphylaxis, hepatic eosinophilic infiltration.

Psychiatric disorders: agitation including aggressive behavior or hostility, anxiousness, depression, disorientation, disturbance in attention, dream abnormalities, hallucinations, insomnia, irritability, memory impairment, restlessness, somnambulism, suicidal thinking and behavior (including suicide), tic, and tremor [see Boxed Warning, Warnings and Precautions (5.1)].

Nervous system disorders: drowsiness, paraesthesia/hypoesthesia, seizures.

Cardiac disorders: palpitations.

Respiratory, thoracic and mediastinal disorders: epistaxis, pulmonary eosinophilia.

Gastrointestinal disorders: diarrhea, dyspepsia, nausea, pancreatitis, vomiting.

Hepatobiliary disorders: Cases of cholestatic hepatitis, hepatocellular liver-injury, and mixed-pattern liver injury have been reported in patients treated with montelukast sodium tablets. Most of these occurred in combination with other confounding factors, such as use of other medications, or when montelukast sodium tablets were administered to patients who had underlying potential for liver disease such as alcohol use or other forms of hepatitis.

Skin and subcutaneous tissue disorders: angioedema, bruising, erythema multiforme, erythema nodosum, pruritus, Stevens-Johnson syndrome/toxic epidermal necrolysis, urticaria.

Musculoskeletal and connective tissue disorders: arthralgia, myalgia including muscle cramps.

Renal and urinary disorders: enuresis in children.

General disorders and administration site conditions: edema.

Patients with asthma on therapy with montelukast sodium tablets may present with systemic eosinophilia, sometimes presenting with clinical features of vasculitis consistent with Churg-Strauss syndrome, a condition which is often treated with systemic corticosteroid therapy. These events have been sometimesassociated with the reduction of oral corticosteroid therapy. Physicians should be alert to eosinophilia, vasculitic rash, worsening pulmonary symptoms, cardiac complications, and/or neuropathy presenting in their patients [see Warnings and Precautions (5.5)].

7 DRUG INTERACTIONS

No dose adjustment is needed when montelukast sodium tablets are co-administered with theophylline, prednisone, prednisolone, oral contraceptives, terfenadine, digoxin, warfarin, gemfibrozil, itraconazole, thyroid hormones, sedative hypnotics, non-steroidal anti-inflammatory agents, benzodiazepines, decongestants, and Cytochrome P450 (CYP) enzyme inducers [see Clinical Pharmacology (12.3)].

8 USE IN SPECIFIC POPULATIONS

8.1 Pregnancy

Risk Summary

Available data from published prospective and retrospective cohort studies over decades with montelukast use in pregnant women have not established a drug-associated risk of major birth defects [see Data]. In animal reproduction studies, no adverse developmental effects were observed with oral administration of montelukast to pregnant rats and rabbits during organogenesis at doses approximately 100 and 110 times, respectively, the maximum recommended human daily oral dose (MRHDOD) based on AUCs [see Data].

The estimated background risk of major birth defects and miscarriage for the the indicated population is unknow. All pregnancies have a background risk of birth defect, loss, or other adverse outcomes. In the U.S. general population, the estimated background risk of major birth defects and miscarriage in clinically recognized pregnancies is 2 to 4% and 15 to 20%, respectively.

Clinical Considerations

Disease-associated maternal and/or embryo/fetal risk

Poorly or moderately controlled asthma in pregnancy increases the maternal risk of perinatal adverse outcomes such as preeclampsia and infant prematurity, low birth weight, and small for gestational age.

Data

Human Data

Published data from prospective and retrospective cohort studies have not identified an association with montelukast sodium use during pregnancy and major birth defects. Available studies have methodologic limitations, including small sample size, in some cases retrospective data collection, and inconsistent comparator groups.

Animal Data

In embryo-fetal development studies, montelukast administered to pregnant rats and rabbits during organogenesis (gestation days 6 to 17 in rats and 6 to 8 in rabbits) did not cause any adverse developmental effects at maternal oral doses up to 400 and 300 mg/kg/day in rats and rabbits, respectively (approximately 100 and 110 times the AUC in humans at the MRHDOD, respectively).

8.2 Lactation

Risk Summary

A published clinical lactation study reports the presence of montelukast in human milk. Data available on the effects of the drug on infants, either directly [see Use in Specific Populations (8.4)] or through breast milk, do not suggest a significant risk of adverse events from exposure to montelukast sodium. The effects of the drug on milk production are unknown. The developmental and health benefits of breastfeeding should be considered along with the mother’s clinical need for montelukast sodium and any potential adverse effects on the breastfed infant from montelukast sodium or from the underlying maternal condition.

8.4 Pediatric Use

The safety and effectiveness in pediatric patients below the age of 12 months with asthma, 6 months with perennial allergic rhinitis, and 6 years with exercise-induced bronchoconstriction have not been established.

8.5 Geriatric Use

Of the total number of subjects in clinical studies of montelukast, 3.5% were 65 years of age and over, and 0.4% were 75 years of age and over. No overall differences in safety or effectiveness were observed between these subjects and younger subjects, and other reported clinical experience has not identified differences in responses between the elderly and younger patients, but greater sensitivity of some older individuals cannot be ruled out. The pharmacokinetic profile and the oral bioavailability of a single 10 mg oral dose of montelukast are similar in elderly and younger adults. The plasma half-life of montelukast is slightly longer in the elderly. No dosage adjustment in the elderly is required.

8.6 Hepatic Insufficiency

No dosage adjustment is required in patients with mild-to-moderate hepatic insufficiency [see Clinical Pharmacology (12.3)].

8.7 Renal Insufficiency

No dosage adjustment is recommended in patients with renal insufficiency [see Clinical Pharmacology (12.3)].

10 OVERDOSAGE

No specific information is available on the treatment of overdosage with montelukast sodium. In the event of overdose, it is reasonable to employ the usual supportive measures; e.g., remove unabsorbed material from the gastrointestinal tract, employ clinical monitoring, and institute supportive therapy, if required. It is not known whether montelukast is removed by peritoneal dialysis or hemodialysis.

11 DESCRIPTION

Montelukast sodium USP, the active ingredient in montelukast sodium tablets, is a selective and orally active leukotriene receptor antagonist that inhibits the cysteinyl leukotriene CysLT1 receptor.

Montelukast sodium USP is described chemically as [ R-(E)]-1-[[[1-[3-[2-(7-chloro-2-quinolinyl)ethenyl]phenyl]-3-[2-(1-hydroxy-1-methylethyl)phenyl]propyl]thio]methyl] cyclopropaneacetic acid, monosodium salt.

The empirical formula is C35H35CINNaO3S, and its molecular weight is 608.17. The structural formula is:

Montelukast sodium USP is a hygroscopic, optically active, white or almost white powder. Montelukast sodium USP is freely soluble in water and methylene chloride, freely soluble to very soluble in alcohol.

Each 10 mg film-coated montelukast sodium tablet contains 10.4 mg montelukast sodium USP, which is equivalent to 10 mg of montelukast, and the following inactive ingredients: croscarmellose sodium, hydroxypropyl cellulose, lactose monohydrate, magnesium stearate, mannitol and microcrystalline cellulose. The tablets are coated with opadry yellow which contains carnauba wax, hydroxypropyl cellulose, hypromellose, red iron oxide, titanium dioxide and yellow iron oxide.

12 CLINICAL PHARMACOLOGY

12.1 Mechanism of Action

The cysteinyl leukotrienes (LTC4, LTD4, LTE4) are products of arachidonic acid metabolism and are released from various cells, including mast cells and eosinophils. These eicosanoids bind to cysteinyl leukotriene (CysLT) receptors. The CysLT type-1. (CysLT1) receptor is found in the human airway (including airway smooth muscle cells and airway macrophages) and on other pro-inflammatory cells (including eosinophils and certain myeloid stem cells). CysLTs have been correlated with the pathophysiology of asthma and allergic rhinitis. In asthma, leukotriene-mediated effects include airway edema, smooth muscle contraction, and altered cellular activity associated with the inflammatory process. In allergic rhinitis, CysLTs are released from the nasal mucosa after allergen exposure during both early-and late-phase reactions and are associated with symptoms of allergic rhinitis.
Montelukast is an orally active compound that binds with high affinity and selectivity to the CysLT1receptor (in preference to other pharmacologically important airway receptors, such as the prostanoid, cholinergic, or β-adrenergic receptor). Montelukast inhibits physiologic actions of LTD4at the CysLT1receptor without any agonist activity.

12.2 Pharmacodynamics

Montelukast causes inhibition of airway cysteinyl leukotriene receptors as demonstrated by the ability to inhibit bronchoconstriction due to inhaled LTD4in asthmatics. In a placebo-controlled, crossover study (n=12), montelukast sodium tablets inhibited early- and late-phase bronchoconstriction due to antigen challenge by 75% and 57%, respectively.

The effect of montelukast sodium tablets on eosinophils in the peripheral blood was examined in clinical trials. In patients with asthma aged 15 years and older who received montelukast sodium tablets, a decrease in mean peripheral blood eosinophil counts ranging from 9% to 15% was noted, compared with placebo, over the double-blind treatment periods. In patients with seasonal allergic rhinitis aged 15 years and older who received montelukast sodium tablets, a mean increase of 0.2% in peripheral blood eosinophil counts was noted, compared with a mean increase of 12.5% in placebo-treated patients, over the double-blind treatment periods; this reflects a mean difference of 12.3% in favor of montelukast sodium tablets. The relationship between these observations and the clinical benefits of montelukast noted in the clinical trials is not known [see Clinical Studies (14)].

12.3 Pharmacokinetics

Absorption

Montelukast is rapidly absorbed following oral administration. After administration of the 10 mg film-coated tablet to fasted adults, the mean peak montelukast plasma concentration (Cmax) is achieved in 3 to 4 hours (Tmax). The mean oral bioavailability is 64%. The oral bioavailability and Cmaxare not influenced by a standard meal in the morning.

The safety and efficacy of montelukast sodium tablets in patients with asthma were demonstrated in clinical trials in which the 10 mg film-coated tablet formulation was administered in the evening without regard to the time of food ingestion. The safety and efficacy of montelukast sodium tablets in patients with seasonal allergic rhinitis were demonstrated in clinical trials in which the 10 mg film-coated tablet was administered in the morning or evening without regard to the time of food ingestion.

The comparative pharmacokinetics of montelukast when administered as two 5 mg chewable tablets versus one 10 mg film-coated tablet have not been evaluated.

Distribution

Montelukast is more than 99% bound to plasma proteins. The steady state volume of distribution of montelukast averages 8 to 11 liters. Studies in rats with radiolabeled montelukast indicate minimal distribution across the blood-brain barrier. In addition, concentrations of radiolabeled material at 24 hours postdose were minimal in all other tissues.

Metabolism

Montelukast is extensively metabolized. In studies with therapeutic doses, plasma concentrations of metabolites of montelukast are undetectable at steady state in adults and pediatric patients

In vitrostudies using human liver microsomes indicate that CYP3A4, 2C8, and 2C9 are involved in the metabolism of montelukast. At clinically relevant concentrations, 2C8 appears to play a major role in the metabolism of montelukast.

Elimination

The plasma clearance of montelukast averages 45 mL/min in healthy adults. Following an oral dose of radiolabeled montelukast, 86% of the radioactivity was recovered in 5-day fecal collections and <0.2% was recovered in urine. Coupled with estimates of montelukast oral bioavailability, this indicates that montelukast and its metabolites are excreted almost exclusively via the bile.

In several studies, the mean plasma half-life of montelukast ranged from 2.7 to 5.5 hours in healthy young adults. The pharmacokinetics of montelukast are nearly linear for oral doses up to 50 mg. During once-daily dosing with 10 mg montelukast, there is little accumulation of the parent drug in plasma (14%).

Special Populations

Hepatic Insufficiency:Patients with mild-to-moderate hepatic insufficiency and clinical evidence of cirrhosis had evidence of decreased metabolism of montelukast resulting in 41 % (90% CI=7%, 85%) higher mean montelukast AUC following a single 10 mg dose. The elimination of montelukast was slightly prolonged compared with that in healthy subjects (mean half-life, 7.4 hours). No dosage adjustment is required in patients with mild-to-moderate hepatic insufficiency. The pharmacokinetics of montelukast sodium tablets in patients with more severe hepatic impairment or with hepatitis have not been evaluated.

Renal Insufficiency:Since montelukast and its metabolites are not excreted in the urine, the pharmacokinetics of montelukast were not evaluated in patients with renal insufficiency. No dosage adjustment is recommended in these patients.

Gender:The pharmacokinetics of montelukast are similar in males and females.

Race:Pharmacokinetic differences due to race have not been studied.

Adolescents:Pharmacokinetic studies evaluated the systemic exposure of the 10 mg film-coated tablets in young adults and adolescents ≥15 years of age.

The plasma concentration profile of montelukast following administration of the 10 mg film-coated tablet is similar in adolescents ≥15 years of age and young adults. The 10 mg film-coated tablet is recommended for use in patients ≥15 years of age.

Drug-Drug Interactions

Theophylline, Prednisone, and Prednisolone: Montelukast sodium tablets have been administered with other therapies routinely used in the prophylaxis and chronic treatment of asthma with no apparent increase in adverse reactions. In drug-interaction studies, the recommended clinical dose of montelukast did not have clinically important effects on the pharmacokinetics of the following drugs: theophylline, prednisone, and prednisolone.

Montelukast at a dose of 10 mg once daily dosed to pharmacokinetic steady state, did not cause clinically significant changes in the kinetics of a single intravenous dose of theophylline [predominantly a cytochrome P450 (CYP) 1A2 substrate]. Montelukast at doses of ≥ 100 mg daily dosed to pharmacokinetic steady state, did not cause any clinically significant change in plasma profiles of prednisone or prednisolone following administration of either oral prednisone or intravenous prednisolone.
Oral Contraceptives, Terfenadine, Digoxin, and Warfarin:In drug interaction studies, the recommended clinical dose of montelukast did not have clinically important effects on the pharmacokinetics of the following drugs: oral contraceptives (norethindrone 1 mg/ ethinyl estradiol 35 mcg), terfenadine, digoxin, and warfarin. Montelukast at doses of ≥100 mg daily dosed to pharmacokinetic steady state did not significantly alter the plasma concentrations of either component of an oral contraceptive containing norethindrone 1 mg/ethinyl estradiol 35 mcg. Montelukast at a dose of 10 mg once daily dosed to pharmacokinetic steady state did not change the plasma concentration profile of terfenadine (a substrate of CYP3A4) or fexofenadine, the carboxylates metabolite, and did not prolong the QTc interval following co-administration with terfenadine 60 mg twice daily; did not change the pharmacokinetic profile or urinary excretion of immunoreactive digoxin; did not change the pharmacokinetic profile of warfarin (primarily a substrate of CYP2C9, 3A4 and 1A2) or influence the effect of a single 30 mg oral dose of warfarin on prothrombin time or the International Normalized Ratio (INR).

Thyroid Hormones, Sedative Hypnotics, Non-Steroidal Anti-Inflammatory Agents, Benzodiazepines, and Decongestants:Although additional specific interaction studies were not performed, montelukast sodium tablets were used concomitantly with a wide range of commonly prescribed drugs in clinical studies without evidence of clinical adverse interactions. These medications included thyroid hormones, sedative hypnotics, non-steroidal anti-inflammatory agents, benzodiazepines, and decongestants.

Cytochrome P450 (CYP) Enzyme Inducers:Phenobarbital, which induces hepatic metabolism, decreased the area under the plasma concentration curve (AUC) of montelukast approximately 40% following a single 10 mg dose of montelukast. No dosage adjustment for montelukast sodium tablets is recommended. It is reasonable to employ appropriate clinical monitoring when potent CYP enzyme inducers, such as phenobarbital or rifampin, are co-administered with montelukast sodium tablets.

Effect of Montelukast on Cytochrome P450 (CYP) Enzymes:Montelukast is a potent inhibitor of CYP2C8 in vitro. However, data from a clinical drug-drug interaction study involving montelukast and rosiglitazone (a probe substrate representative of drugs primarily metabolized by CYP2C8) in 12 healthy individuals demonstrated that the pharmacokinetics of rosiglitazone are not altered when the drugs are coadministered, indicating that montelukast does not inhibit CYP2C8 in vivo. Therefore, montelukast is not anticipated to alter the metabolism of drugs metabolized by this enzyme (e.g., paclitaxel, rosiglitazone, and repaglinide). Based on further in vitroresults in human liver microsomes, therapeutic plasma concentrations of montelukast do not inhibit CYP 3A4, 2C9, 1A2, 2A6, 2C19, or 2D6.

Cytochrome P450 (CYP) Enzyme Inhibitors: In vitrostudies have shown that montelukast is a substrate of CYP 2C8, 2C9, and 3A4. Co-administration of montelukast with itraconazole, a strong CYP 3A4 inhibitor, resulted in no significant increase in the systemic exposure of montelukast. Data from a clinical drug-drug interaction study involving montelukast and gemfibrozil (an inhibitor of both CYP 2C8 and 2C9) demonstrated that gemfibrozil, at a therapeutic dose, increased the systemic exposure of montelukast by 4.4-fold. Co-administration of itraconazole, gemfibrozil, and montelukast did not further increase the systemic exposure of montelukast. Based on available clinical experience, no dosage adjustment of montelukast is required upon co-administration with gemfibrozil [see Overdosage (10)] .

13 NONCLINICAL TOXICOLOGY

13.1 Carcinogenesis & Mutagenesis & Impairment Of Fertility

No evidence of tumorigenicity was seen in carcinogenicity studies of either 2 years in Sprague-Dawley rats or 92 weeks in mice at oral gavage doses up to 200 mg/kg/day or 100 mg/kg/day, respectively. The estimated exposure in rats was approximately 120 times the AUC for adults at the maximum recommended daily oral dose. The estimated exposure in mice was approximately 45 times the AUC for adults at the maximum recommended daily oral dose.
Montelukast demonstrated no evidence of mutagenic or clastogenic activity in the following assays: the microbial mutagenesis assay, the V-79 mammalian cell mutagenesis assay, the alkaline elution assay in rat hepatocytes, the chromosomal aberration assay in Chinese hamster ovary cells, and in the in vivomouse bone marrow chromosomal aberration assay.

In fertility studies in female rats, montelukast produced reductions in fertility and fecundity indices at an oral dose of 200 mg/kg (estimated exposure was approximately 70 times the AUC for adults at the maximum recommended daily oral dose). No effects on female fertility or fecundity were observed at an oral dose of 100 mg/kg (estimated exposure was approximately 20 times the AUC for adults at the maximum recommended daily oral dose).Montelukast had no effects on fertility in male rats at oral doses up to 800 mg/kg (estimated exposure was approximately 160 times the AUC for adults at the maximum recommended daily oral dose).

14 CLINICAL STUDIES

14.1 Asthma

Adults and Adolescents 15 Years of Age and Older with Asthma
Clinical trials in adults and adolescents 15 years of age and older demonstrated there is no additional clinical benefit to montelukast doses above 10 mg once daily.

The efficacy of montelukast sodium tablets for the chronic treatment of asthma in adults and adolescents 15 years of age and older was demonstrated in two (U.S. and Multinational) similarly designed, randomized, 12-week, double-blind, placebo-controlled trials in 1576 patients (795 treated with montelukast sodium tablets, 530 treated with placebo, and 251 treated with active control). The median age was 33 years (range 15 to 85); 56.8% were females and 43.2% were males. The ethnic/racial distribution in these studies was 71.6% Caucasian, 17.7% Hispanic, 7.2% other origins and 3.5% Black. Patients had mild or moderate asthma and were non-smokers who required approximately 5 puffs of inhaled β-agonist per day on an "as-needed" basis. The patients had a mean baseline percent of predicted forced expiratory volume in 1 second (FEV1) of 66% (approximate range, 40 to 90%). The co-primary endpoints in these trials were FEV1and daytime asthma symptoms. In both studies after 12 weeks, a random subset of patients receiving montelukast sodium tablets were switched to placebo for an additional 3 weeks of double-blind treatment to evaluate for possible rebound effects.

The results of the U.S. trial on the primary endpoint, morning FEV1, expressed as mean percent change from baseline averaged over the 12-week treatment period, are shown in FIGURE 2. Compared with placebo, treatment with one montelukast sodium (equivalent to10 mg montelukast) tablet daily in the evening resulted in a statistically significant increase in FEV1percent change from baseline (13.0%-change in the group treated with montelukast sodium tablets vs. 4.2%-change in the placebo group, p<0.001); the change from baseline in FEV1for montelukast sodium tablets were 0.32 liters compared with 0.10 liters for placebo, corresponding to a between-group difference of 0.22 liters (p<0.001, 95% CI 0.17 liters, 0.27 liters). The results of the Multinational trial on FEV1were similar.

Figure 2: FEV1Mean Percent Change from Baseline

(U.S. Trial: Montelukast sodium tablets N=406; Placebo N=270)

(ANOVA Model)

The effect of montelukast sodium tablets on other primary and secondary endpoints, represented by the Multinational study is shown in TABLE 2. Results on these endpoints were similar in the US study.

Table 2: Effect of Montelukast Sodium tablets on Primary and Secondary Endpoints in a Multinational Placebo-controlled Trial (ANOVA Model)

 | Montelukast sodium tablets |  |  | Placebo
Endpoint | N | Baseline | Mean Change from Baseline | N | Baseline | Mean Change from Baseline
Daytime Asthma Symptoms (0 to 6 scale) | 372 | 2.35 | -0.49* | 245 | 2.40 | -0.26
β-agonist (puffs per day) | 371 | 5.35 | -1.65* | 241 | 5.78 | -0.42
AM PEFR (L/min) | 372 | 339.57 | 25.03* | 244 | 335.24 | 1.83
PM PEFR (L/min) | 372 | 355.23 | 20.13* | 244 | 354.02 | -0.49
Nocturnal Awakenings (#/week) | 285 | 5.46 | -2.03* | 195 | 5.57 | -0.78

* p<0.001, compared with placebo

Both studies evaluated the effect of montelukast sodium tablets on secondary outcomes, including asthma attack (utilization of health-care resources such as an unscheduled visit to a doctor's office, emergency room, or hospital; or treatment with oral, intravenous, or intramuscular corticosteroid), and use of oral corticosteroids for asthma rescue. In the Multinational study, significantly fewer patients (15.6% of patients) on montelukast sodium tablets experienced asthma attacks compared with patients on placebo (27.3%, p < 0.001). In the US study, 7.8% of patients on montelukast sodium tablets and 10.3% of patients on placebo experienced asthma attacks, but the difference between the two treatment groups was not significant (p = 0.334). In the Multinational study, significantly fewer patients (14.8% of patients) on montelukast sodium tablets were prescribed oral corticosteroids for asthma rescue compared with patients on placebo (25.7%, p < 0.001). In the US study, 6.9% of patients on montelukast sodium tablets and 9.9% of patients on placebo were prescribed oral corticosteroids for asthma rescue, but the difference between the two treatment groups was not significant (p = 0.196).

Onset of Action and Maintenance of Effects

In each placebo-controlled trial in adults, the treatment effect of montelukast sodium tablets, measured by daily diary card parameters, including symptom scores, "as-needed" β-agonist use, and PEFR measurements, was achieved after the first dose and was maintained throughout the dosing interval (24 hours). No significant change in treatment effect was observed during continuous once-daily evening administration in non-placebo-controlled extension trials for up to one year. Withdrawal of montelukast sodium tablets in asthmatic patients after 12 weeks of continuous use did not cause rebound worsening of asthma.

Effects in Patients on Concomitant Inhaled Corticosteroids

Separate trials in adults evaluated the ability of montelukast sodium tablets to add to the clinical effect of inhaled corticosteroids and to allow inhaled corticosteroid tapering when used concomitantly.

One randomized, placebo-controlled, parallel-group trial (n=226) enrolled adults with stable asthma with a mean FEV1of approximately 84% of predicted who were previously maintained on various inhaled corticosteroids (delivered by metered-dose aerosol or dry powder inhalers). The median age was 41.5 years (range 16 to 70); 52.2% were females and 47.8% were males. The ethnic/racial distribution in this study was 92.0% Caucasian, 3.5% Black, 2.2% Hispanic, and 2.2% Asian. The types of inhaled corticosteroids and their mean baseline requirements included beclomethasone dipropionate (mean dose, 1203 mcg/day), triamcinolone acetonide (mean dose, 2004 mcg/day), flunisolide (mean dose, 1971 mcg/day), fluticasone propionate (mean dose, 1083 mcg/day), or budesonide (mean dose, 1192 mcg/day). Some of these inhaled corticosteroids were non-U.S.-approved formulations, and doses expressed may not be ex-actuator. The pre-study inhaled corticosteroid requirements were reduced by approximately 37% during a 5- to 7-week placebo run-in period designed to titrate patients toward their lowest effective inhaled corticosteroid dose. Treatment with montelukast sodium tablets resulted in a further 47% reduction in mean inhaled corticosteroid dose compared with a mean reduction of 30% in the placebo group over the 12-week active treatment period (p≤0.05). It is not known whether the results of this study can be generalized to patients with asthma who require higher doses of inhaled corticosteroids or systemic corticosteroids.

In another randomized, placebo-controlled, parallel-group trial (n=642) in a similar population of adult patients previously maintained, but not adequately controlled, on inhaled corticosteroids (beclomethasone 336 mcg/day), the addition of montelukast sodium tablets to beclomethasone resulted in statistically significant improvements in FEV1compared with those patients who were continued on beclomethasone alone or those patients who were withdrawn from beclomethasone and treated with montelukast or placebo alone over the last 10 weeks of the 16-week, blinded treatment period. Patients who were randomized to treatment arms containing beclomethasone had statistically significantly better asthma control than those patients randomized to montelukast sodium tablets alone or placebo alone as indicated by FEV1, daytime asthma symptoms, PEFR, nocturnal awakenings due to asthma, and "as-needed" β-agonist requirements.

In adult patients with asthma with documented aspirin sensitivity, nearly all of whom were receiving concomitant inhaled and/or oral corticosteroids, a 4-week, randomized, parallel-group trial (n=80) demonstrated that montelukast sodium tablets, compared with placebo, resulted in significant improvement in parameters of asthma control. The magnitude of effect of montelukast sodium tablets in aspirin-sensitive patients was similar to the effect observed in the general population of asthma patients studied. The effect of montelukast sodium tablets on the bronchoconstrictor response to aspirin or other non-steroidal anti-inflammatory drugs in aspirin-sensitive asthmatic patients has not been evaluated [ see Warnings and Precautions (5.4)].

14.2 Exercise-Induced Bronchoconstriction (EIB)

Exercise-Induced Bronchoconstriction (Adults and Adolescents 15 years of age and older)

The efficacy of montelukast sodium (equivalent to10 mg montelukast) tablets, when given as a single dose 2 hours before exercise for the prevention of EIB was investigated in three (U.S. and Multinational), randomized, double-blind, placebo-controlled crossover studies that included a total of 160 adult and adolescent patients 15 years of age and older with EIB. Exercise challenge testing was conducted at 2 hours, 8.5 or 12 hours, and 24 hours following administration of a single dose of study drug (montelukast sodium [equivalent to10 mg montelukast] tablets or placebo). The primary endpoint was the mean maximum percent fall in FEV1following the 2 hours post-dose exercise challenge in all three studies (Study A, Study B, and Study C). In Study A, a single dose of montelukast sodium (equivalent to 10 mg montelukast) tablets demonstrated a statistically significant protective benefit against EIB when taken 2 hours prior to exercise. Some patients were protected from EIB at 8.5 and 24 hours after administration; however, some patients were not. The results for the mean maximum percent fall at each timepoint in Study A are shown in TABLE 3 and are representative of the results from the other two studies.

Table 3: Mean Maximum Percent Fall in FEV1Following Exercise
Challenge in Study A (N=47)
ANOVA Model

Time of exercise challenge following medication administration | Mean Maximum percent fall in FEV1* |  | Treatment difference % for Montelukast sodium tablets versus Placebo (95%CI)*
 | Montelukast sodium tablets | Placebo
2 hours | 13 | 22 | -9 (-12, -5)
8.5 hours | 12 | 17 | -5 (-9, -2)
24 hours | 10 | 14 | -4 (-7, -1)

*Least squares-mean

Daily administration of montelukast sodium tablets for the chronic treatment of asthma has not been established to prevent acute episodes of EIB.

In a 12-week, randomized, double-blind, parallel group study of 110 adult and adolescent asthmatics 15 years of age and older, with a mean baseline FEV1percent of predicted of 83% and with documented exercise-induced exacerbation of asthma, treatment with montelukast sodium (equivalent to 10 mg montelukast) tablets, once daily in the evening, resulted in a statistically significant reduction in mean maximal percent fall in FEV1and mean time to recovery to within 5% of the pre-exercise FEV1. Exercise challenge was conducted at the end of the dosing interval (i.e., 20 to 24 hours after the preceding dose). This effect was maintained throughout the 12-week treatment period indicating that tolerance did not occur. Montelukast sodium tablets did not, however, prevent clinically significant deterioration in maximal percent fall in FEV1after exercise (i.e., ≥20% decrease from pre-exercise baseline) in 52% of patients studied. In a separate crossover study in adults, a similar effect was observed after two once-daily 10 mg doses of montelukast sodium.

14.3 Allergic Rhinitis (Seasonal and Perennial)

Seasonal Allergic Rhinitis

The efficacy of montelukast sodium tablets for the treatment of seasonal allergic rhinitis was investigated in 5 similarly designed, randomized, double-blind, parallel-group, placebo- and active-controlled (loratadine) trials conducted in North America. The 5 trials enrolled a total of 5029 patients, of whom 1799 were treated with montelukast sodium tablets. Patients were 15 to 82 years of age with a history of seasonal allergic rhinitis, a positive skin test to at least one relevant seasonal allergen, and active symptoms of seasonal allergic rhinitis at study entry.

The period of randomized treatment was 2 weeks in 4 trials and 4 weeks in one trial. The primary outcome variable was mean change from baseline in daytime nasal symptoms score (the average of individual scores of nasal congestion, rhinorrhea, nasal itching, sneezing) as assessed by patients on a 0 to 3 categorical scale.

Four of the five trials showed a significant reduction in daytime nasal symptoms scores with montelukast sodium (equivalent to 10 mg montelukast) tablets compared with placebo. The results of one trial are shown below. The median age in this trial was 35.0 years (range 15 to 81); 65.4% were females and 34.6% were males. The ethnic/racial distribution in this study was 83.1% Caucasian, 6.4% other origins, 5.8% Black, and 4.8% Hispanic. The mean changes from baseline in daytime nasal symptoms score in the treatment groups that received montelukast sodium tablets, loratadine, and placebo are shown in TABLE 5. The remaining three trials that demonstrated efficacy showed similar results.

Table 5: Effects of Montelukast Sodium tablets on Daytime Nasal Symptoms Score*

in a Placebo- and Active-controlled Trial in Patients with Seasonal Allergic Rhinitis

(ANCOVA Model)

Treatment Group (N) | Baseline Mean Score | Mean Change from Baseline | Difference Between Treatment and Placebo (95% CI) Least-Squares Mean
Montelukast sodium tablets (equivalent to 10 mg montelukast) (344) | 2.09 | -0.39 | -0.13†(-0.21, -0.06)
Placebo (351) | 2.10 | -0.26 | N.A
Active Control‡ (Loratadine 10 mg) (599) | 2.06 | -0.46 | -0.24†(-0.31, -0.17)

* Average of individual scores of nasal congestion, rhinorrhea, nasal itching, sneezing as assessed by

patients on a 0 to 3 categorical scale.

† Statistically different from placebo (p≤0.001).

‡The study was not designed for statistical comparison between montelukast sodium and the active control (loratadine).

Perennial Allergic Rhinitis

The efficacy of montelukast sodium tablets for the treatment of perennial allergic rhinitis was investigated in 2 randomized, double-blind, placebo-controlled studies conducted in North America and Europe. The two studies enrolled a total of 3357 patients, of whom 1632 received montelukast sodium (equivalent to 10 mg montelukast) tablets. Patients 15 to 82 years of age with perennial allergic rhinitis as confirmed by history and a positive skin test to at least one relevant perennial allergen (dust mites, animal dander, and/or mold spores), who had active symptoms at the time of study entry, were enrolled.

In the study in which efficacy was demonstrated, the median age was 35 years (range 15 to 81); 64.1% were females and 35.9% were males. The ethnic/racial distribution in this study was 83.2% Caucasian, 8.1% Black, 5.4% Hispanic, 2.3% Asian, and 1.0% other origins. Montelukast sodium (equivalent to 10 mg montelukast) tablets once daily was shown to significantly reduce symptoms of perennial allergic rhinitis over a 6-week treatment period (TABLE 6); in this study the primary outcome variable was mean change from baseline in daytime nasal symptoms score (the average of individual scores of nasal congestion, rhinorrhea, and sneezing).

Table 6: Effects of Montelukast Sodium tablets on Daytime Nasal Symptoms Score* in a Placebo-controlled Trial in Patients with Perennial Allergic Rhinitis

(ANCOVA Model)

Treatment Group (N) | Baseline Mean Score | Mean Change from Baseline | Difference Between Treatment and Placebo (95% CI) Least-Squares Mean
Montelukast sodium tablets (equivalent to 10 mg montelukast) (1000) | 2.09 | -0.42 | - 0.08†(-0.12, -0.04)
Placebo (980) | 2.10 | -0.35 | NA

*Average of individual scores of nasal congestion, rhinorrhea, sneezing as assessed by patients on a 0 to 3 categorical scale.

†Statistically different from placebo (p≤0.001).

The other 6-week study evaluated montelukast sodium (equivalent to 10 mg montelukast) tablets (n=626), placebo (n=609), and an active-control (cetirizine 10 mg; n=120). The primary analysis compared the mean change from baseline in day time nasal symptoms score for montelukast sodium tablets vs. placebo over the first 4 weeks of treatment; the study was not designed for statistical comparison between montelukast sodium tablets and the active-control. The primary outcome variable included nasal itching in addition to nasal congestion, rhinorrhea, and sneezing. The estimated difference between montelukast sodium tablets and placebo was -0.04 with a 95% CI of (-0.09, 0.01). The estimated difference between the active-control and placebo was -0.10 with a 95% CI of (-0.19, -0.01).

16 HOW SUPPLIED/STORAGE AND HANDLING

Montelukast sodium (equivalent to 10 mg montelukast) tablets are beige, rounded square-shaped, film coated tablets debossed with 'I' on one side and '114' on the other side. They are supplied as follows:

Unit of Use Bottles of 30 NDC 68645-560-54

Storage

Store at 20° to 25° C (68° to 77° F) [see USP Controlled Room Temperature].Protect from moisture and light. Store in original container. When product container is subdivided, repackage into a well-closed, light-resistance container.

17 PATIENT COUNSELING INFORMATION

For the tablets, advise the patient and/or caregiver to read the FDA-approved patient labeling (Medication Guide).

- Advise patients about the potential risk for serious neuropsychiatric symptoms and behavioral changes with montelukast sodium use.
- Discuss the benefits and risks of montelukast sodium with patients when prescribing or continuing treatment with montelukast sodium.
- Advise patients to monitor for changes in behavior or neuropsychiatric symptoms inpatients taking montelukast sodium.
- Instruct patients to discontinue montelukast sodium and contact a healthcare provider immediately if changes in behavior or thinking that are not typical for the patient occur, or if the patient develops suicidal ideation or suicidal behavior.
- Advise patients to take montelukast sodium daily as prescribed, even when they are asymptomatic, as well as during periods of worsening asthma, and the contact their physicians if their asthma is not well controlled.
- Advise Patients that oral montelukast sodium is not for the treatment of acute asthma attacks. They should have appropriate short-acting inhaled β-agonist. Daily administration of montelukast sodium tablets for the chronic treatment of asthma has not been established to prevent acute episodes of EIB.
- Advise patients to seek medical attention if short-acting inhaled bronchodilators are needed more often than usual, or if more than the maximum number of inhalations of short-acting bronchodilator treatment prescribed for a 24-hour period are needed.
- Instruct patients to continue other anti-asthma medications as prescribed unless instructed by a physician.
- Instruct patients with known aspirin sensitivity to continue avoidance of aspirin or non-steroidal anti-inflammatory agents while taking montelukast sodium.

Manufactured for:
Camber Pharmaceuticals Inc.
Piscataway, NJ 08854

By: HETEROTM
Hetero Labs Limited Unit V, Polepally,
Jadcherla, Mahaboob Nagar – 509 301, India.

Revised: 08/2020

Packaged by:
Legacy Pharmaceutical Packaging LLC
Earth City, MO 63045

Distributed by:
The Kroger Co.
Cincinnati, OH 45202

PATIENT INFORMATION

Montelukast Sodium Tablets
(mon” te loo’ kast soe’ dee um)

What is the most important information I should know about montelukast sodium tablets?

Serious mental health problems have happened in people taking montelukast sodium tabletsor even after treatment has stopped. This can happen in people with or without a history of mental health problems. Stop taking montelukast sodium tablets and tell your healthcare provider right away if you or your child have any unusual changes in behavior or thinking, including any of these symptoms:

- agitation, including aggressive behavior or hostility
- attention problems
- bad or vivid dreams
- depression
- disorientation (confusion)
- feeling anxious
- irritability
- hallucinations (seeing or hearing things that are not really there)
- memory problems
- obsessive-compulsive symptoms
- restlessness
- sleep walking
- stuttering
- suicidal thoughts and actions (including suicide)
- tremor
- trouble sleeping
- uncontrolled muscle movements

What are montelukast sodium tablets?

Montelukast sodium tablets are a prescription medicine that blocks substances in the body called leukotrienes. This may help to improve symptoms of asthma and inflammation of the lining of the nose (allergic rhinitis). Montelukast sodium tablets do not contain a steroid.

Montelukast sodium tablets are used to:

1. Prevent asthma attacks and for the long-term treatment of asthma in adults and adolescents ages 15 years

and older.
Do not take montelukast sodium tablets if you need relief right away for a sudden asthma attack.If you
have an asthma attack, you should follow the instructions your healthcare provider gave you for treating
asthma attacks.

2. Prevent exercise-induced asthma in people 15 years of age and older.

3. Help control the symptoms of allergic rhinitis such as sneezing, stuffy nose, runny nose, and itching of
the nose. Montelukast sodium tablets are used to treat the following in people who have already taken
other medicines that did not work well enough or in people who could not tolerate other medicines:

- outdoor allergies that happen part of the year (seasonal allergic rhinitis) in adults and adolescents

ages 15 years and older, and

- indoor allergies that happen all year (perennial allergic rhinitis) in adults and adolescents

ages 15 years and older.

Do nottake montelukast sodium tablets if you are allergic to any of its ingredients. See the end of this Medication Guide for a complete list of the ingredients in montelukast sodium tablets.

Before taking montelukast sodium tablets, tell your healthcare provider about all your medical conditions, including if you:

- are allergic to aspirin.
- have or have had mental health problems.
- are pregnant or plan to become pregnant. Talk to your healthcare provider if you are pregnant or plan to become pregnant, montelukast sodium tablets may not be right for you.
- are breastfeeding or plan to breastfeed. It is not known if montelukast sodium passes into your breast milk. Talk to your healthcare provider about the best way to feed your baby while taking montelukastsodium tablets.

Tell your healthcare provider about all the medicines you take, including prescription and over the counter medicines, vitamins, and herbal supplements. Some medicines may affect how montelukast sodium tablets work, or montelukast sodium tablets may affect how your other medicines work.

How should I take montelukast sodium tablets?

For anyonewho takes montelukast sodium tablets:
• Take montelukast sodium tablets exactly as prescribed by your healthcare provider. Your healthcareprovider will tell you how much montelukast sodium tablets to take, and when to take it.
• Stop taking montelukast sodium tablets and tell your healthcare provider right away if you or your child have any unusual changes in behavior or thinking.
• You can take montelukast sodium tablets with food or without food.
• If you or your child misses a dose of montelukast sodium tablets, just take the next dose at yourregular time.Do not take 2 doses at the same time.
• If you take too much montelukast sodium, call your healthcare provider right away.

For adults and adolescents 15 years of age and older with asthma:

• Take montelukast sodium tablets 1 time each day, in the evening. Continue to take montelukast sodium tablets every day for as long as your healthcare provider prescribes it, even if you have no asthmasymptoms.
• Tell your healthcare provider right away if your asthma symptoms get worse, or if you need to use your rescue inhaler medicine more often for asthma attacks.
• Always have your rescue inhaler medicine with you for asthma attacks.
• Continue to take your other asthma medicines as prescribed unless your healthcare provider tells you to change how you take these medicines.

For people 15 years of age and older for the prevention of exercise-induced asthma:

• Take montelukast sodium tablets at least 2 hours before exercise.
• Always have your rescue inhaler medicine with you for asthma attacks.
• If you take montelukast sodium tablets every day for chronic asthma or allergic rhinitis, do not takeanother dose to prevent exercise-induced asthma. Talk to your healthcare provider about your treatment for exercise-induced asthma.
• Do not take 2 doses of montelukast sodium tablets within 24 hours (1 day).

For anyone 15 years of age and older with seasonal allergic rhinitis, or for anyone 15 years of age and older with perennial allergic rhinitis:

• Take montelukast sodium tablets 1 time each day, at about the same time each day.

What should I avoid while taking montelukast sodium tablets?

If you have asthma and aspirin makes your asthma symptoms worse, continue to avoid taking aspirin or other medicines called non-steroidal anti-inflammatory drugs (NSAIDs) while taking montelukast sodium tablets.

What are the possible side effects of montelukast sodium tablets?

Montelukast sodium tablets may cause serious side effects, including:

• See “What is the most important information I should know about montelukast sodium tablets?”

• Increase in certain white blood cells (eosinophils) and possible inflamed blood vessels throughout the body (systemic vasculitis).Rarely, this can happen in people with asthma who take montelukastsodium tablets. This sometimes happens in people who also take a steroid medicine by mouth that is being stopped or the dose is being lowered.

Tell your healthcare provider right away if you get one or more of these symptoms:

- a feeling of pins and needles or numbness of arms or legs
- a flu-like illness
- rash
- severe inflammation (pain and swelling) of the sinuses (sinusitis)

The most common side effects of montelukast sodium tablets include:
• upper respiratory infection
• fever
• headache
• sore throat
• cough
• stomach pain
• diarrhea
• earache or ear infection
• flu
• runny nose
• sinus infection
These are not all the possible side effects of montelukast sodium tablets. Call your doctor for medical advice about side effects. You may report side effects to FDA at 1-800-FDA-1088.

How should I store montelukast sodium tablets?

• Store montelukast sodium tablets at room temperature between 68° to 77°F (20° to 25°C).
• Keep montelukast sodium tablets in the package they come in.
• Keep montelukast sodium tablets in a dry place and keep it away from light.
• Keep montelukast sodium tablets and all medicines out of reach of children.
General information about the safe and effective use of montelukast sodium tablets.

Medicines are sometimes prescribed for purposes other than those listed in a Medication Guide. Do not use montelukast sodium tablets for a condition for which it was not prescribed. Do not give montelukast sodium tablets to other people even if they have the same symptoms you have. It may harm them.

You can ask your pharmacist or healthcare provider for information about montelukast sodium tablets that is written for health professionals.

For more information, call Hetero Labs Limited at 1-866-495-1995.
What are the ingredients in montelukast sodium tablets?

Active ingredient:montelukast sodium USP

Inactive ingredients:croscarmellose sodium, hydroxypropyl cellulose, lactose monohydrate, magnesium stearate, mannitol and microcrystalline cellulose. The tablets are coated with opadry yellow which contains carnauba wax, hydroxypropyl cellulose, hypromellose, red iron oxide, titanium dioxide and yellow iron oxide.

This Medication Guide has been approved by the U.S. Food and Drug Administration

Medication Guide available at http://camberpharma.com/medication-guides

Manufactured for:
Camber Pharmaceuticals Inc.
Piscataway, NJ 08854

By: HETEROTM
Hetero Labs Limited Unit V, Polepally,
Jadcherla, Mahaboob Nagar – 509 301, India.

Revised: 08/2020

Packaged by:
Legacy Pharmaceutical Packaging LLC
Earth City, MO 63045

Distributed by:
The Kroger Co.
Cincinnati, OH 45202

PACKAGE LABEL.PRINCIPAL DISPLAY PANEL

Montelukast Sodium Tablets, 10 mg